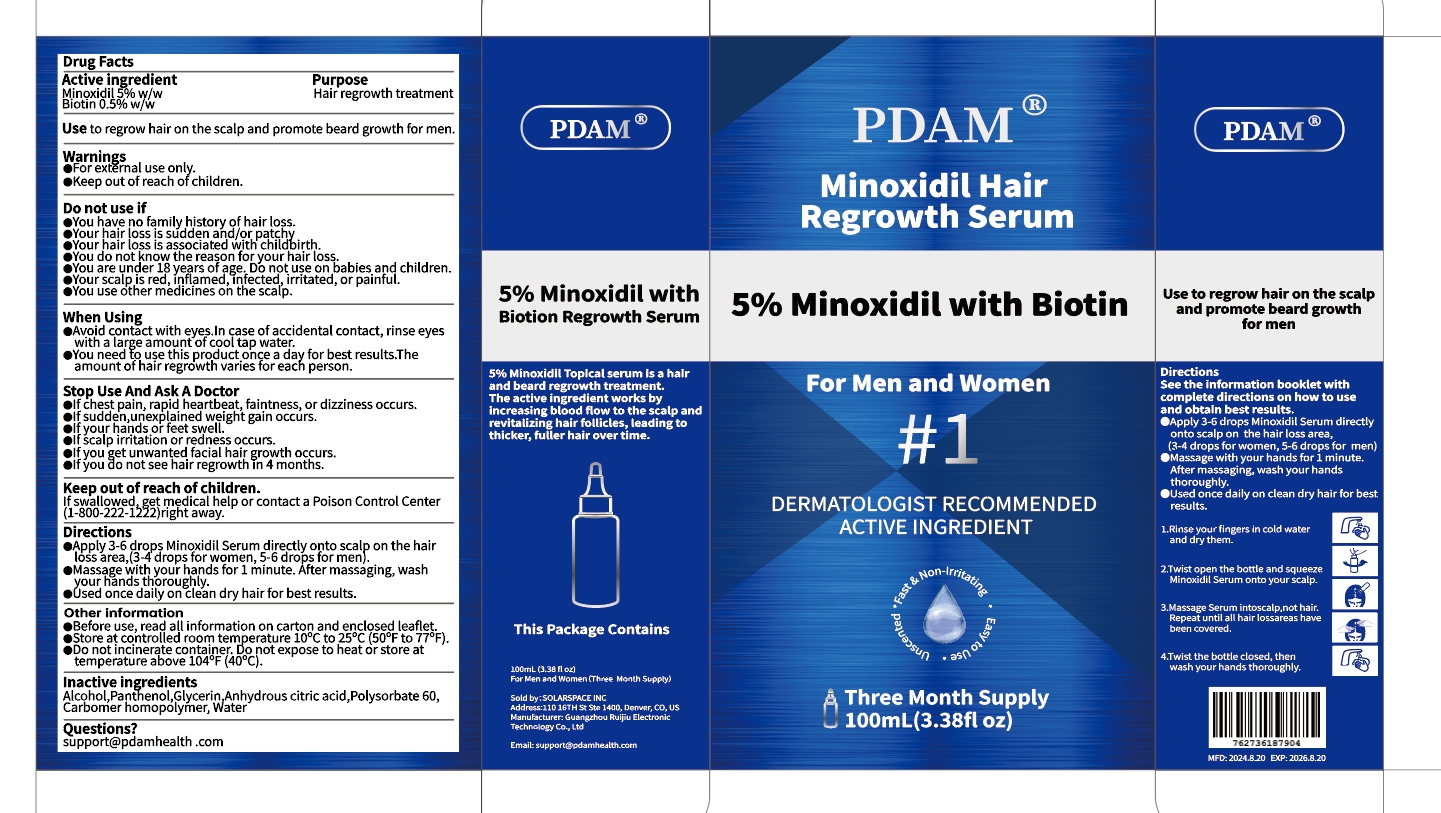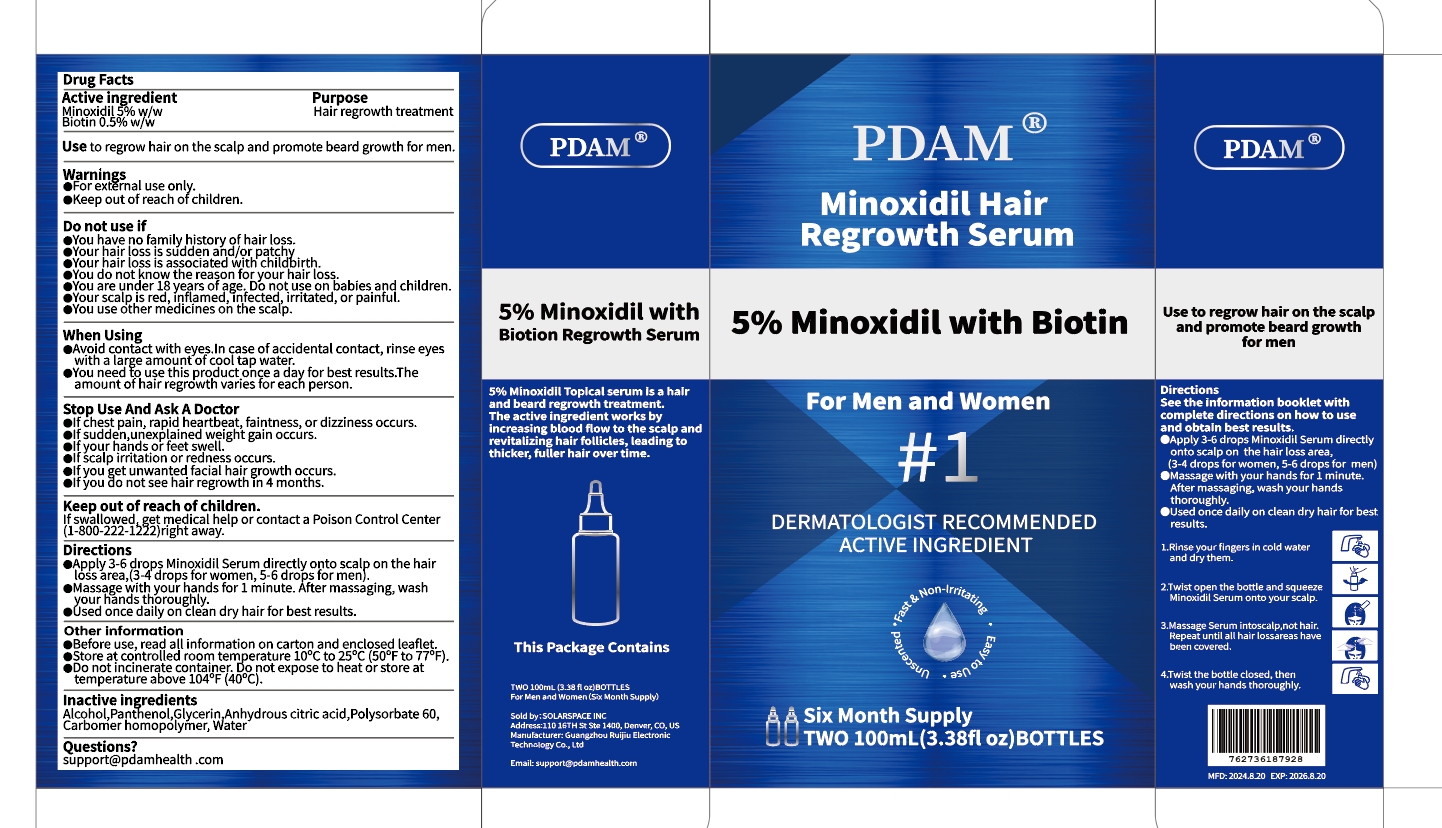 DRUG LABEL: 5% Minoxidil Hair Regrowth Serum With Biotin
NDC: 83767-401 | Form: LIQUID
Manufacturer: Guangzhou Ruijiu Electronic Technology Co., Ltd.
Category: otc | Type: HUMAN OTC DRUG LABEL
Date: 20240819

ACTIVE INGREDIENTS: BIOTIN 0.5 g/100 mL; MINOXIDIL 5 g/100 mL
INACTIVE INGREDIENTS: POLYSORBATE 60; GLYCERIN; ANHYDROUS CITRIC ACID; WATER; ALCOHOL; PANTHENOL; CARBOMER HOMOPOLYMER, UNSPECIFIED TYPE

5% Minoxidil Hair Regrowth Serum With Biotin

5% Minoxidil Hair Regrowth Serum With Biotin

ACTIVE INGREDIENT

Minoxidil 5%
Biotin 0.5%

PURPOSE

Hair regrowth treatment

INDICATIONS AND USAGE

Use to regrow hair on the scalp and promote beard growth for men.

WARNINGS

For extérnal use only.
Keep out of reach of children.

DO NOT USE

You have no family history of hair loss.
Your halr loss is sudden and/or patchy.
Your hair loss is associated with childbirth.
You do not know the reason for your hair loss.
You are under 18 years of age, Do not use on babies and children.
Your scalp is red, inflamed,infected, irritated, or painful.
You use other medicines on the scalp.

WHEN USING

Avoid contact with eyes.In case of accidental contact, rinse eyeswith a large amountof cool tap water.
You need fo use this product once a day for best results.Theamount of hair regrowth varies for each person.

STOP USE

lf chest pain, rapid heartbeat, faintness, or dizziness occurs.
lf sudden,unexplained weight gain occurs.
lf your hands or feet swell.
if scalp irritation or redness occurs.
lf you get unwanted facial hair growth occurs.
lf you do not see hair regrowth in 4 months.

KEEP OUT OF REACH OF CHILDREN

lf swallowed,get medical help or contact a Poison Control Center (1-800-222-1222)right away.

DOSAGE AND ADMINISTRATION

Apply3-6 drops Minoxidil Serum directly onto scalp on the hair loss area,(3-4 drops for women, 5-6 drops for men).
Massage with your hands for 1 minute. After massaging, wash your hands thoroughly.
Used once daily on clean dry hair for best results.

STORAGE AND HANDLING

Before use, read all information on carton and enclosed leaflet.Store at controlled room temperature 10'C to 25°℃ (50°F to 77°F)Do not incinerate container. Do not expose to heat or store attemperature above 104°F(40°C)

INACTIVE INGREDIENT

Alcohol
Panthenol
Glycerin
Anhydrous citric acid
Polysorbate 60
Carbomer homopolymer
Water